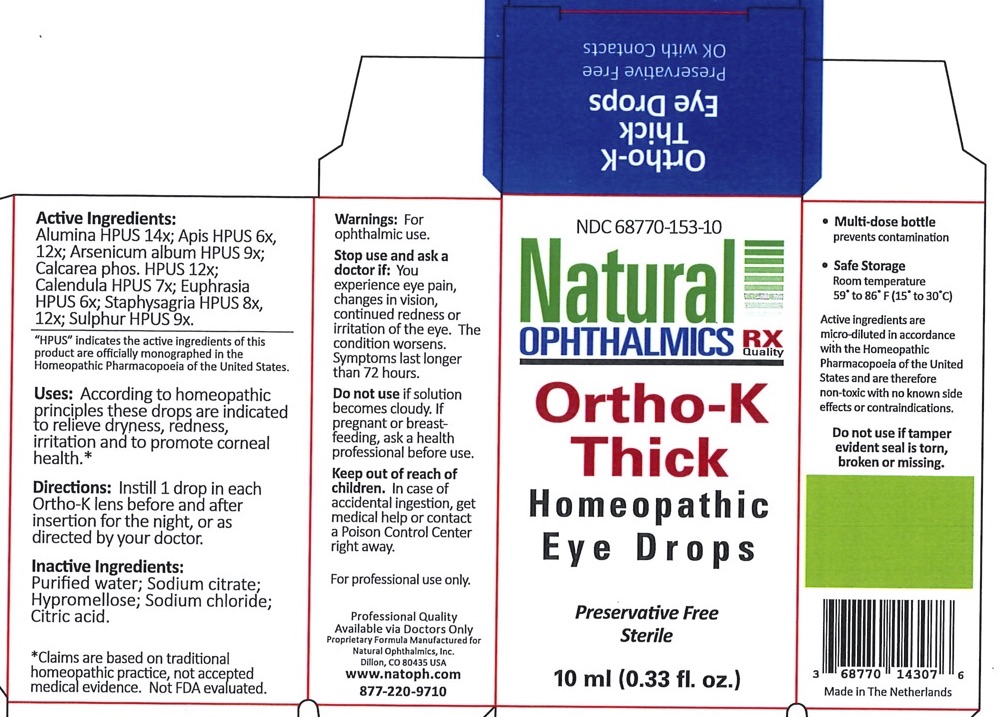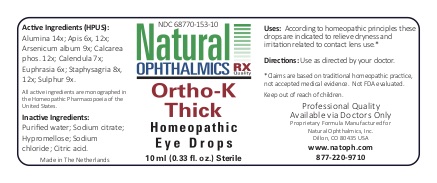 DRUG LABEL: Ortho-K Thick
NDC: 68770-153 | Form: LIQUID
Manufacturer: Natural Ophthalmics, Inc
Category: homeopathic | Type: HUMAN OTC DRUG LABEL
Date: 20220707

ACTIVE INGREDIENTS: ALUMINUM OXIDE 14 [hp_X]/1 mL; APIS MELLIFERA 6 [hp_X]/1 mL; ARSENIC TRIOXIDE 9 [hp_X]/1 mL; CALENDULA OFFICINALIS FLOWERING TOP 7 [hp_X]/1 mL; TRIBASIC CALCIUM PHOSPHATE 12 [hp_X]/1 mL; EUPHRASIA STRICTA 6 [hp_X]/1 mL; DELPHINIUM STAPHISAGRIA SEED 8 [hp_X]/1 mL; SULFUR 9 [hp_X]/1 mL
INACTIVE INGREDIENTS: HYPROMELLOSES; WATER; POLYSORBATE 80; CITRIC ACID MONOHYDRATE; SODIUM CHLORIDE

Ortho-K Thick

Homeopathic Purpose

Alumina | 14x | Dryness of the eyes and other mucous membranes
Apis | 6x & 12x | Pain, redness, edema, allergies
Arsenicum album | 9x | Severe dryness
Calendula | 7x | Corneal healing/vitality
Calcarea phosphorica | 12X | Foreign body sensation
Euphrasia (Eyebright) | 6x | General dryness, redness and irritation of the eye and lids
Staphysagria | 8x & 12x | Foreign body sensation
Sulphur | 9x | Dryness, redness of eye and lid, allergies

Active Ingredients

Alumina | 14x
Apis | 6x & 12x
Arsenicum album | 9x
Calendula | 7x
Calcarea phosphorica | 12X
Euphrasia (Eyebright) | 6x
Staphysagria | 8x & 12x
Sulphur | 9x

"HPUS" indicates the active ingredients of this product are officially monographed in the Homeopathic Pharmacopoeia of the United States.

Inactive Ingredients

Purified water, Polysorbate 80, Sodium citrate, Sodium chloride, Citric acid, Hypromellos

Uses

According to homeopathic principles these drops are indicated to relieve dryness, redness, irritation and to promote corneal health.*

*Claims are based on traditional homeopathic practice, not accepted medical evidence. Not FDA evaluated.

Directions

Instill 1 drop in each Ortho-K lens before and after insertion for the night, or as directed by your doctor.

Warnings

- For ophthalmic use.
- For Professional Use Only

Do not use if tamper evident seal is torn, broken. or missing.

Stop use and ask a doctor if: You experience eye pain, changes in vision, continued redness or irritation of the eye. The condition worsens. Symptoms last longer than 72 hours.

Keep out of reach of children.

In case of accidental ingestion, get medical help or contact a Poison Control Center right away.

If pregnant or breast feeding, ask a health professional before use.

Do not use if solution becomes cloudy.

Storage

- Safe Storage

Room temperature.
59o to 86o (15o to 30o C)

QUESTIONS

Natural Ophthalmics, Inc.
Lafayette, CO 80026 USA
www.natoph.com
877-220-9710